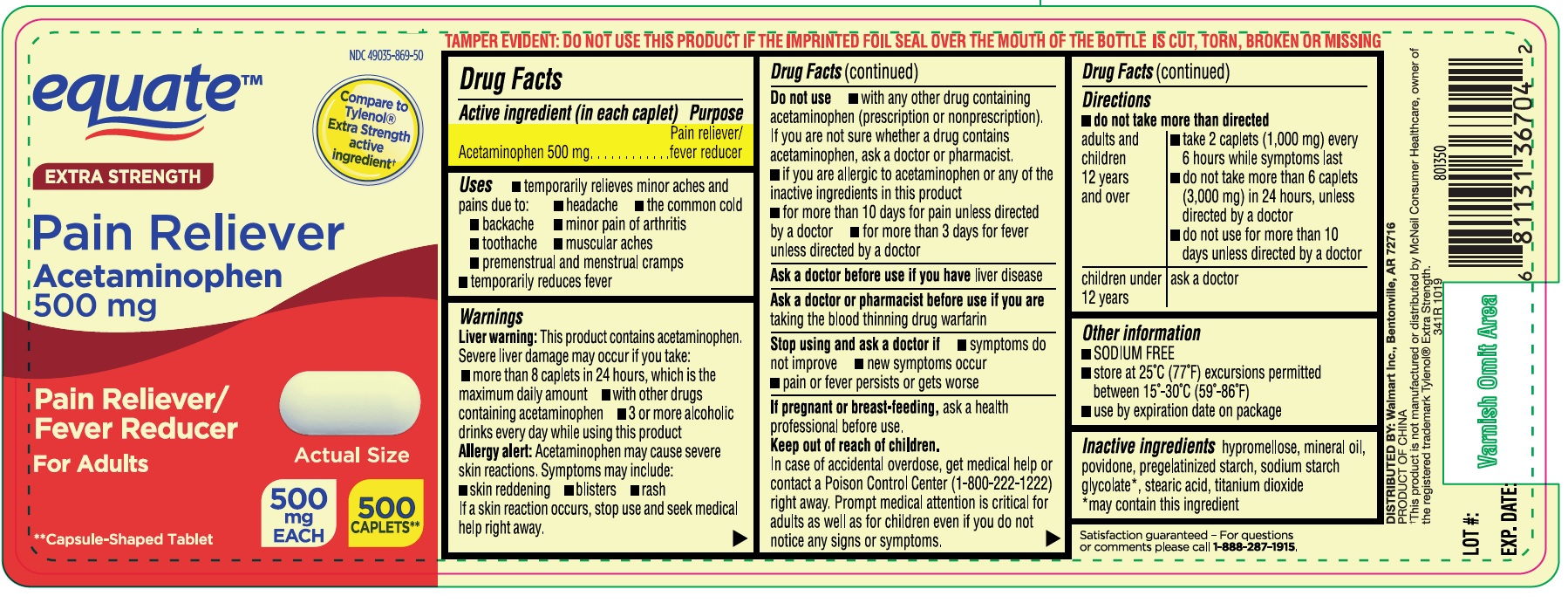 DRUG LABEL: ACETAMINOPHEN
NDC: 49035-869 | Form: TABLET, COATED
Manufacturer: WAL-MART STORES INC
Category: otc | Type: HUMAN OTC DRUG LABEL
Date: 20250111

ACTIVE INGREDIENTS: ACETAMINOPHEN 500 mg/1 1
INACTIVE INGREDIENTS: HYPROMELLOSES; POVIDONE; STARCH, CORN; STEARIC ACID; TITANIUM DIOXIDE; SODIUM STARCH GLYCOLATE TYPE A CORN; MINERAL OIL

341R Walmart Acetaminophen 500 mg Tablets (49035-869)

Active ingredient (in each caplet)

Acetaminophen 500 mg

Purpose

Pain reliever/fever reducer

Uses

temporarily relieves minor aches and pains due to:

- headache
- the common cold
- backache
- minor pain of arthritis
- toothache
- muscular aches
- premenstrual and menstrual cramps

temporarily reduces fever

Warnings

Liver warning: This product contains acetaminophen. Severe liver damage may occur if you take

- more than 8 caplets in 24 hours, which is the maximum daily amount
- with other drugs containing acetaminophen
- 3 or more alcoholic drinks every day while using this product

Allergy alert: Acetaminophen may cause severe skin reactions. Symptoms may include:

- skin reddening
- blisters
- rash

If a skin reaction occurs, stop use and seek medical help right away.

Do not use

- with any other drug containing acetaminophen (prescription or nonprescription). If you are not sure whether a drug contains acetaminophen, ask a doctor or pharmacist.
- if you are allergic to acetaminophen or any of the inactive ingredients in this product
- for more than 10 days for pain unless directed by a doctor
- for more than 3 days for fever unless directed by a doctor

Ask a doctor before use if you have liver disease

Ask a doctor or pharmacist before use if you are taking the blood thinning drug warfarin

Stop using and ask a doctor if

- symptoms do not improve
- new symptoms occur
- pain or fever persists or gets worse

PREGNANCY OR BREAST FEEDING

If pregnant or breast-feeding, ask a health professional before use.

Keep out of reach of children.

In case of accidental overdose, get medical help or contact a Poison Control Center right away (1-800-222-1222) right away. Prompt medical attention is critical for adults as well as for children even if you do not notice any signs or symptoms.

Directions

do not take more than directed.

adults and children 12 years and over:

- take 2 caplets (1,000 mg) every 6 hours while symptoms last
- do not take more than 6 caplets (3,000 mg) in 24 hours, unless directed by a doctor

- do not use more than 10 days unless directed by a doctor

children under 12 years:ask a doctor

Other information

- SODIUM FREE
- store at 25°C (77°F) excursions permitted between 15-30°C (59-86°F)
- use by expiration date on package

Inactive ingredients

hypromellose, mineral oil, povidone, pregelatinized starch, sodium starch glycolate*, stearic acid, titanium dioxide

*may contain this ingredient